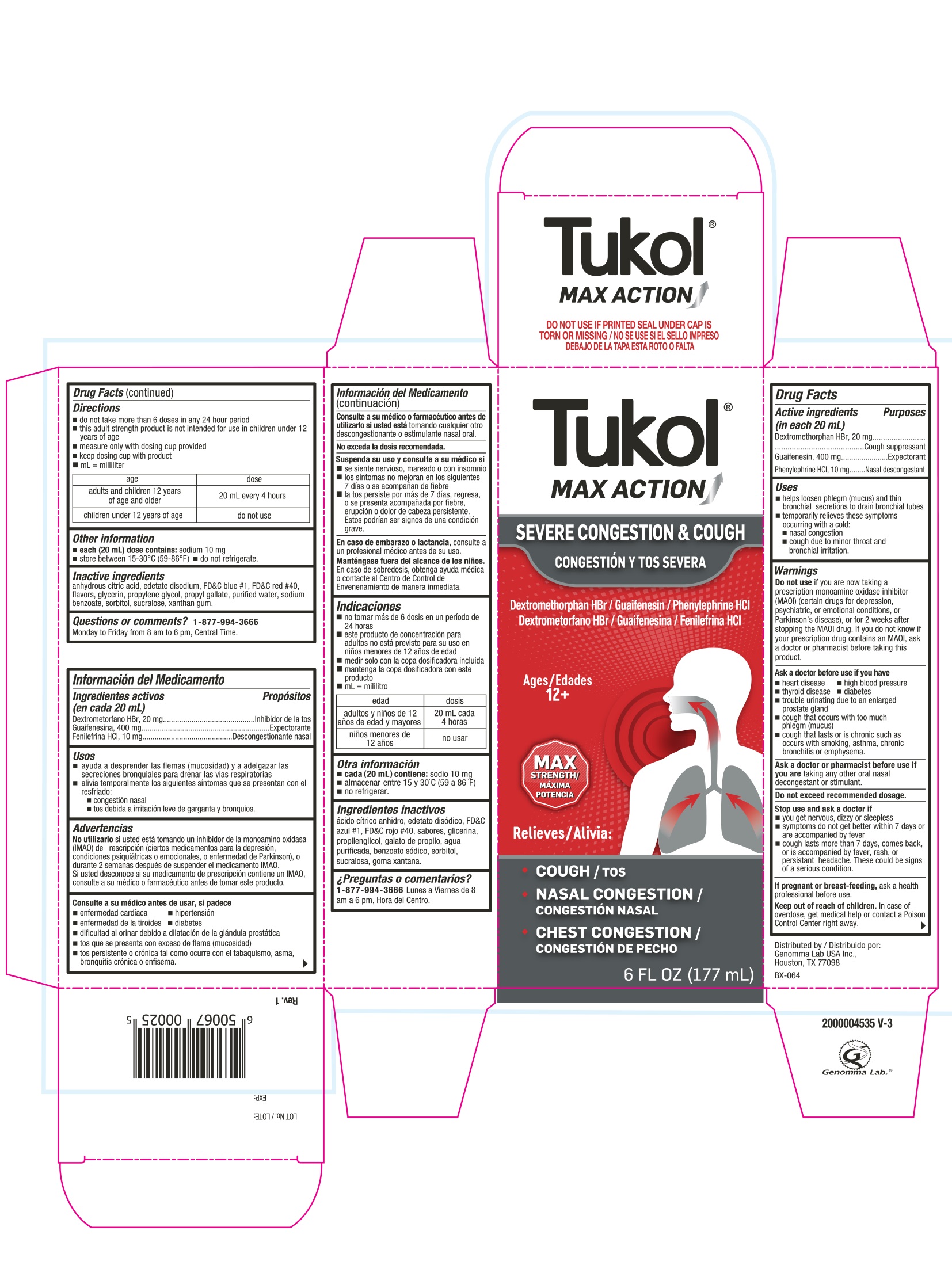 DRUG LABEL: Tukol MAX ACTION Severe Congestion and Cough
NDC: 50066-517 | Form: LIQUID
Manufacturer: Genomma Lab USA, Inc
Category: otc | Type: HUMAN OTC DRUG LABEL
Date: 20241016

ACTIVE INGREDIENTS: DEXTROMETHORPHAN HYDROBROMIDE 20 mg/20 mL; GUAIFENESIN 400 mg/20 mL; PHENYLEPHRINE HYDROCHLORIDE 10 mg/20 mL
INACTIVE INGREDIENTS: ANHYDROUS CITRIC ACID; EDETATE DISODIUM; FD&C BLUE NO. 1; FD&C RED NO. 40; GLYCERIN; PROPYLENE GLYCOL; PROPYL GALLATE; WATER; SODIUM BENZOATE; SORBITOL; SUCRALOSE; XANTHAN GUM

Tukol MAX ACTION Severe Congestion & Cough

Drug Facts Active ingredients (in each 20 mL)

Dextromethorphan HBr 20 mg
Guaifenesin 400 mg
Phenylephrine HCL 10 mg

Purpose

Cough suppressant
Expectorant
Nasal decongestant

Uses

- Helps loosen phlegm (mucus) and thin bronchial secretions to drain bronchial tubes
- temporarily relieves these symptoms occuring with a cold:
- nasal congestion
- cough due to minor throat and bronchial irritation

Warnings

Do not use

- if you are now taking a prescription monoamine oxidase inhibitor (MAOI) (certain drugs for depression, psychiatic, or emotional conditions, or Parkinson's disease), or for 2 weeks after stopping an MAOI drug. If you do not know if your prescription drug contains an MAOI, ask a doctor or pharmacist before taking this product.

Ask a doctor before use if you have

- heart disease
- high blood pressure
- thyroid disease
- diabetes
- trouble urinating due to an enlarged prostate gland
- cough that occurs with too much phlegm (mucus)
- cough that lasts or is chronic such as occurs with smoking, asthma, chronic bronchitis or emphysema

Ask a doctor or pharmacist before use if you are

taking any other oral nasal decongestant or stimulant.

Do not exceed recommended dosage.

Stop use and ask a doctor if

- you get nervous, dizzy or sleepless
- symptoms do not get better within 7 days or are accompanied by fever
- cough lasts more than 7 days, comes back, or is accompanied by fever, rash or persistent headache

These could be signs of a serious condition.

If pregnant or breast-feeding

ask a professional before use

Keep out of reach of children

In case of overdose, get medical help or contact a Poison Control Center right away.

Directions

- Do not take more than 6 doses in any 24 hour period
- this adult stregth product is not intended for use in children under 12 years of age
- measure only with dosing cup provided
- keep dosing cup with product
- mL = mililiter

age | dose
adults and children 12 years of age and older | 20 mL every 4 hours
children under 12 years of age | do not use

Other information

- Each 20 mL dose contains: sodium 10 mg
- store between15-30°C (59-86 °F)
- do not refrigerate

Inactive Ingredients

Anhydrous citric acid, edetate disodium, FD&C Blue # 1, FD&C Red # 40, flavors, glycerin, propylene glycol, propyl gallate, purified water, sodium benzoate, sorbitol, sucralose, xanthan gum

Questions or comments?

1-877-994-3666
Monday to Friday from 8 AM to 6 PM, Central time

Tukol MAX ACTION Severe Congestion & Cough

Tukol® MAX ACTION

DO NOT USE IF PRINTED SEAL UNDER CAP IS TORN OR MISSING

DEXTROMETHORPHAN HBr/GUAIFENESIN/PHENYLEPHRINE HCL

Relieves

- Cough
- Nasal Congestion
- Chest Congestion

Ages 12+

6 FL OZ (177 mL)

Distributed by:
Genomma Lab USA, Inc.
Houston, TX 77098